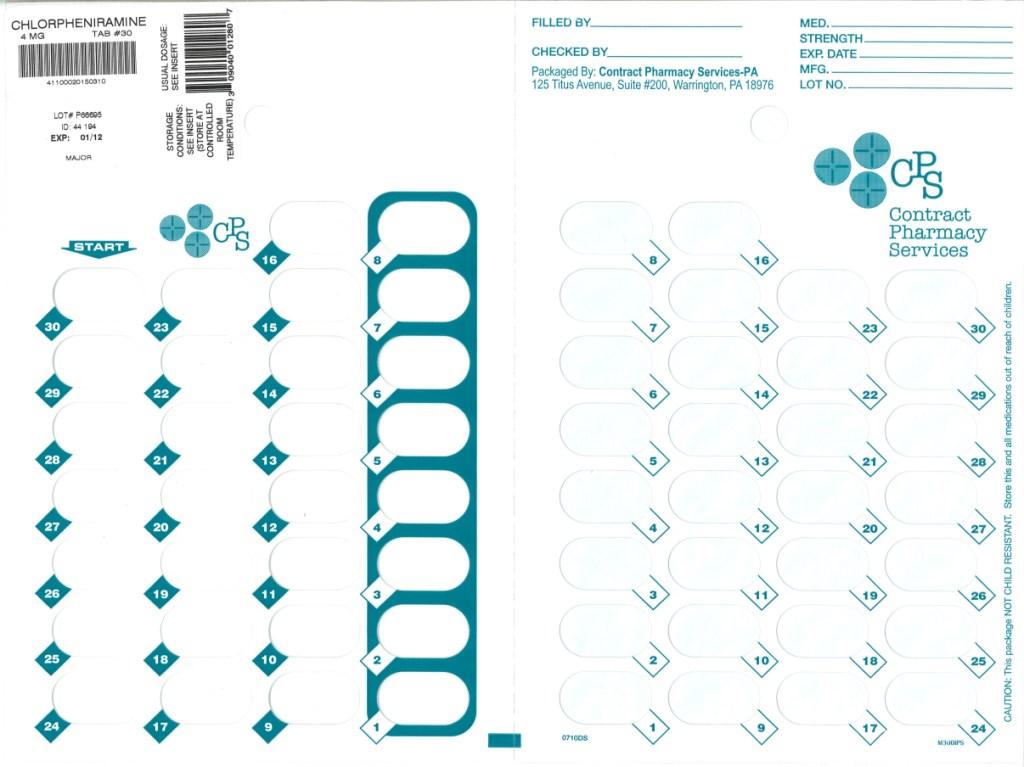 DRUG LABEL: Chlorpheniramine maleate
NDC: 67046-089 | Form: TABLET
Manufacturer: Contract Pharmacy Services-PA
Category: otc | Type: HUMAN OTC DRUG LABEL
Date: 20110110

ACTIVE INGREDIENTS: CHLORPHENIRAMINE MALEATE 4 mg/1 1
INACTIVE INGREDIENTS: D&C YELLOW NO. 10; LACTOSE; MAGNESIUM STEARATE; CELLULOSE, MICROCRYSTALLINE; STARCH, CORN

Chlorpheniramine Maleate

Active ingredient

Chlorpheniramine maleate 4 mg

Purpose

Antihistamine

Uses

- temporarily relieves these symptoms of hay fever or other upper respiratory allergies:
- runny nose
- sneezing
- itchy nose or throat
- itchy, watery eyes

Warnings

Do not use

to make a child sleepy

Ask a doctor before use if you have

- glaucoma
- trouble urinating due to an enlarged prostate gland
- a breathing problem such as emphysema or chronic bronchitis

Ask a doctor or pharmacist before use if you are

taking sedatives or tranquilizers

When using this product

- alcohol, sedatives and tranquilizers may increase drowsiness
- drowsiness may occur
- avoid alcoholic drinks
- excitability may occur, especially in children
- be careful when driving a motor vehicle or operating machinery

If pregnant or breast-feeding,

ask a health professional before use.

Keep out of reach of children.

In case of overdose, get medical help or contact a Poison Control Center right away.

Directions

take every 4 to 6 hours, not more than 6 doses in 24 hours

adults and children 12 years of age and over | 1 tablet (4 mg)
children 6 to under 12 years of age | 1/2 tablet (2 mg)
children 4 to under 6 years of age | do not use unless; directed by a doctor
children under 4 years of age | do not use

Inactive ingredients

D&C yellow #10 lake, lactose, magnesium stearate, microcrystalline cellulose, pregelatinized starch.

QUESTIONS OR COMMENTS?

Distributed by:

Major Pharmaceuticals

31778 Enterprise Drive

Livonia, MI 48150, USA

1-734-743-6000

Repackaged by:
Contract Pharmacy Services-PA
125 Titus Ave Suite 200
Warrington, PA 18976 USA

Original--01/2011--NJW

Package/Label Principal Display Panel

Blister of 30 Tablets